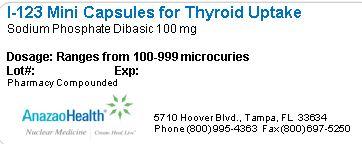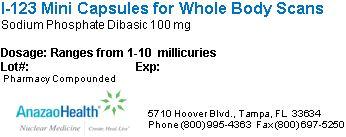 DRUG LABEL: I 123 Mini
NDC: 51808-102 | Form: CAPSULE
Manufacturer: AnazaoHealth Corporation
Category: prescription | Type: HUMAN PRESCRIPTION DRUG LABEL
Date: 20120523

ACTIVE INGREDIENTS: IODIDE ION I-123 10 mCi/1 1
INACTIVE INGREDIENTS: SODIUM PHOSPHATE, DIBASIC 100 mg/1 1

I-123 Mini Caps
Medical Professional Information Sheet

Dear Medical Professional, Per your order, we have compounded I-123 in Mini Cap form. The characteristics of this compound are:

DESCRIPTION

Sodium Iodide I-123 (NaI-123) for diagnostic use is supplied for oral administration in a small opaque white gelatin capsule, which is placed inside a red and clear outer capsule. The capsules are available in strengths up to 10 mCi of I-123 at a specific time. Gelatin capsules are compounded, per prescription requirements, using high specific concentration I-123, allowing higher iodine activity in a small easy to swallow capsule size.The radionuclidic composition at calibration is not less than 97.0 percent I-123, not more than 2.9 percent I-125 and not more than 0.1 percent Te-121. The radionuclidic composition at expiration time is not less than 87.2 percent I-123, not more than 12.4 percent I-125 and not more than 0.4 percent Te-121. The ratio of the concentration of I-123 and I-125 changes with time. Iodine-123 has a physical half-life of 13.2 hours.

INDICATIONS AND USAGE

Administration of Sodium Iodide I-123 is indicated as a diagnostic procedure to be used in evaluating thyroid function and/or morphology

DOSAGE AND ADMINISTRATION

Anti-thyroid therapy of a severely hyperthyroid patient is usually discontinued three to four days before administration of radioiodide. For hyperthyroidism, the usual dose range is 4 to 10 mCi. Toxic nodular goiter and other special situations will require the use of larger doses. For thyroid carcinoma, 50 mCi is the usual dose for ablation of normal thyroid tissue, and 100 to 150 mCi is the usual subsequent therapeutic dose. Waterproof gloves should be used during the entire handling and administration procedure. Adequate shielding must be maintained.

CLINICAL UTILITY

.Sodium Iodide I-123 is readily absorbed from the upper gastrointestinal tract. Following absorption, the iodide is distributed primarily within the extracellular fluid of the body. It is trapped and organically bound by the thyroid and concentrated by the stomach, choroid plexus and salivary glands. It is excreted by the kidneys. The fraction of the administered dose which is accumulated in the thyroid gland may be a measure of thyroid function in the absence of unusually high or low iodine intake or administration of certain drugs which influence iodine accumulation by the thyroid gland. Normal subjects can accumulate approximately 10 to 50% of the administered iodine dose in the thyroid gland, however, the normal and abnormal ranges are established by individual physician’s criteria. The mapping (imaging) of Sodium Iodide I-123 distribution in the thyroid gland may provide useful information concerning thyroid anatomy and definition of normal and/or abnormal functioning of tissue within the gland

Thank you,

AnazaoHealth Corporation